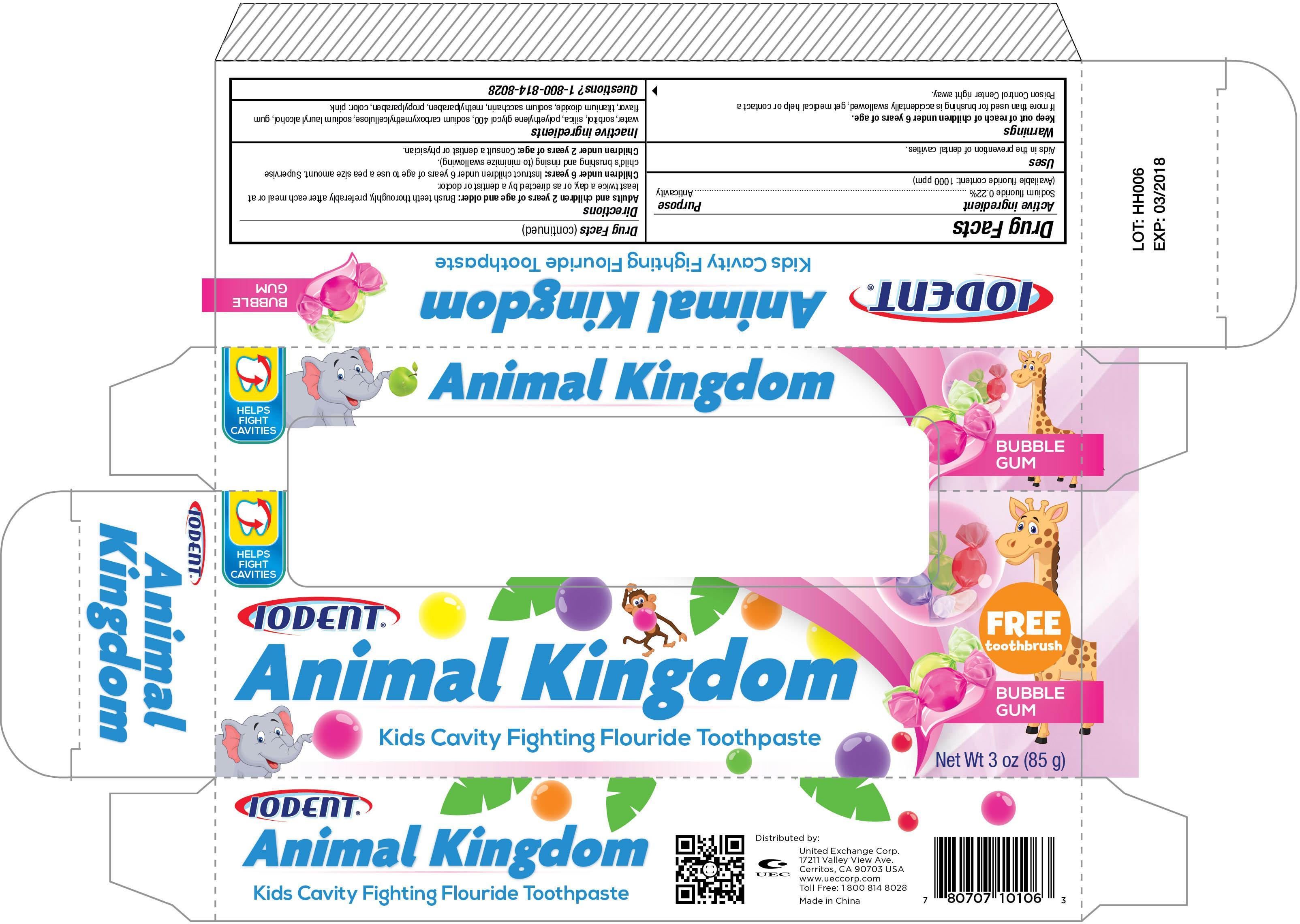 DRUG LABEL: Iodent Animal Kingdom Bubble Gum
NDC: 65923-106 | Form: PASTE
Manufacturer: United Exchange Corp.
Category: otc | Type: HUMAN OTC DRUG LABEL
Date: 20150305

ACTIVE INGREDIENTS: SODIUM FLUORIDE 0.22 g/100 g
INACTIVE INGREDIENTS: WATER; SORBITOL; POLYETHYLENE GLYCOL 400; TITANIUM DIOXIDE; METHYLPARABEN; PROPYLPARABEN

Active Ingredient Purpose

Sodium fluoride 0.22%---------------------------------------------------------------------------Anti-Cavity

(Available fluoride content:1000 ppm)

Uses

Aids in the prevention of dental cavities.

Warnings

If more than used for brushing is accidentally swallowed, get medical help or contact a Poison Control Center right away.

KEEP OUT OF REACH OF CHILDREN

Keep out of the reach of children under 6 years of age.

INDICATIONS AND USAGE

Direction:

Aduts and children 2 years of age and older: Brush teeth thoroughly, preferably after each meal or at least twice a day, or as directed by a dentist or doctor.

Children under 6 years: Instruct children under 6 years of age to use a pea size amount. Supervise child's brushing and rinsing (to minimize swallowing).

Children under 2 years of age: Consult a dentist or physician.

Inactive ingredients

water, sorbitol, silica, polyethylene glycol 400, sodium carboxymethylcellulose, sodium lauryl alcohol, gum flavor, titanium dioxide, sodium saccharin, methylparaben, propylparaben, color: pink

DOSAGE AND ADMINISTRATION

Distributed by:

United Exchange Corp.

17211 Valley View Ave.,

Cerritos, CA 90703 USA